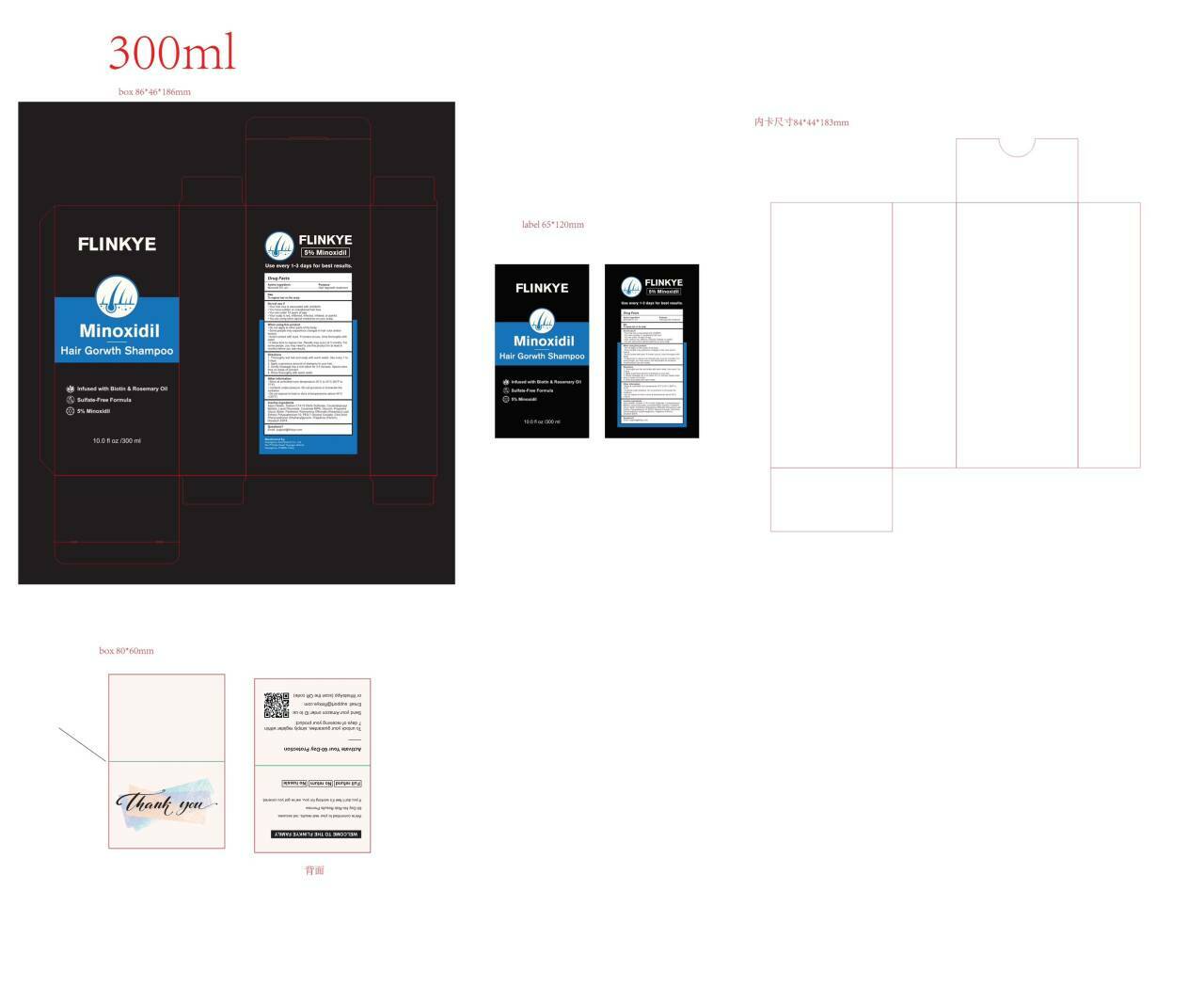 DRUG LABEL: FLINKYE 5% Minoxidil Hair Growth
NDC: 84148-017 | Form: SHAMPOO
Manufacturer: Guangzhou Ariel Biotech Co., Ltd.
Category: otc | Type: HUMAN OTC DRUG LABEL
Date: 20251204

ACTIVE INGREDIENTS: MINOXIDIL 5 g/100 mL
INACTIVE INGREDIENTS: EDETATE DISODIUM; SODIUM C14-16 OLEFIN SULFONATE; COCAMIDOPROPYL BETAINE; LAURYL GLUCOSIDE; COCAMIDE MIPA; GLYCERIN; PROPYLENE GLYCOL; BIOTIN; PANTHENOL; ROSMARINUS OFFICINALIS (ROSEMARY) LEAF POWDER; POLYQUATERNIUM-10 (1000 MPA.S AT 2%); PEG-7 GLYCERYL COCOATE; CITRIC ACID; PHENOXYETHANOL; ETHYLHEXYLGLYCERIN; PARFUMIDINE; AQUA

84148-017

Active Ingredient(s)

Minoxidil 5% w/v

Purpose

Hair regrowth treatment

Use

To regrow hair on the scalp

Warnings

For external use only.

Do not use

.Your hair loss is associated with childbirth.
.You have sudden or unexplained hair loss.
. You are under 18 years of age.
.Your scalp is red, inflamed, infected, irritated, or painful.
·You are using other topical medicines on your scalp.

WHEN USING

. Do not apply to other parts of the body.
. Some people may experience changes in hair color and/or texture.
.Avoid contact with eyes. If contact occurs, rinse thoroughly with water.
.It takes time to regrow hair. Results may occur at 3 months.For
some people, you may need to use this product for at least 6
months before you see results.

Discontinue use if redness or irritation occurs.

Keep out of reach of children.

Directions

1. Thoroughly wet hair and scalp with warm water. Use every 1 to 3 days.
2. Apply a generous amount of shampoo to your hair.
3. Gently massage into a rich lather for 3-5 minutes. Spend extra time on areas of concern.
4. Rinse thoroughly with warm water.

Other information

.Store at controlled room temperature20°C to 25°C (68F to 77°F).
. Contents under pressure. Do not puncture or incinerate the container.

. Do not expose to heat or store at temperatures above 49°C (120°F).

Inactive ingredients

Aqua (Water), Sodium C14-16 Olefin Sulfonate,Cocamidopropyl Betaine, Lauryl Glucoside,CocamideMIPA, Glycerin, Propylene
Glycol, Biotin, Panthenol, Rosmarinus Officinalis (Rosemary) Leaf Extract, Polyquaternium-10, PEG-7 Glyceryl Cocoate, Citric Acid,
Phenoxyethanol, Ethylhexylglycerin, Fragrance (Parfum), Disodium EDTA.